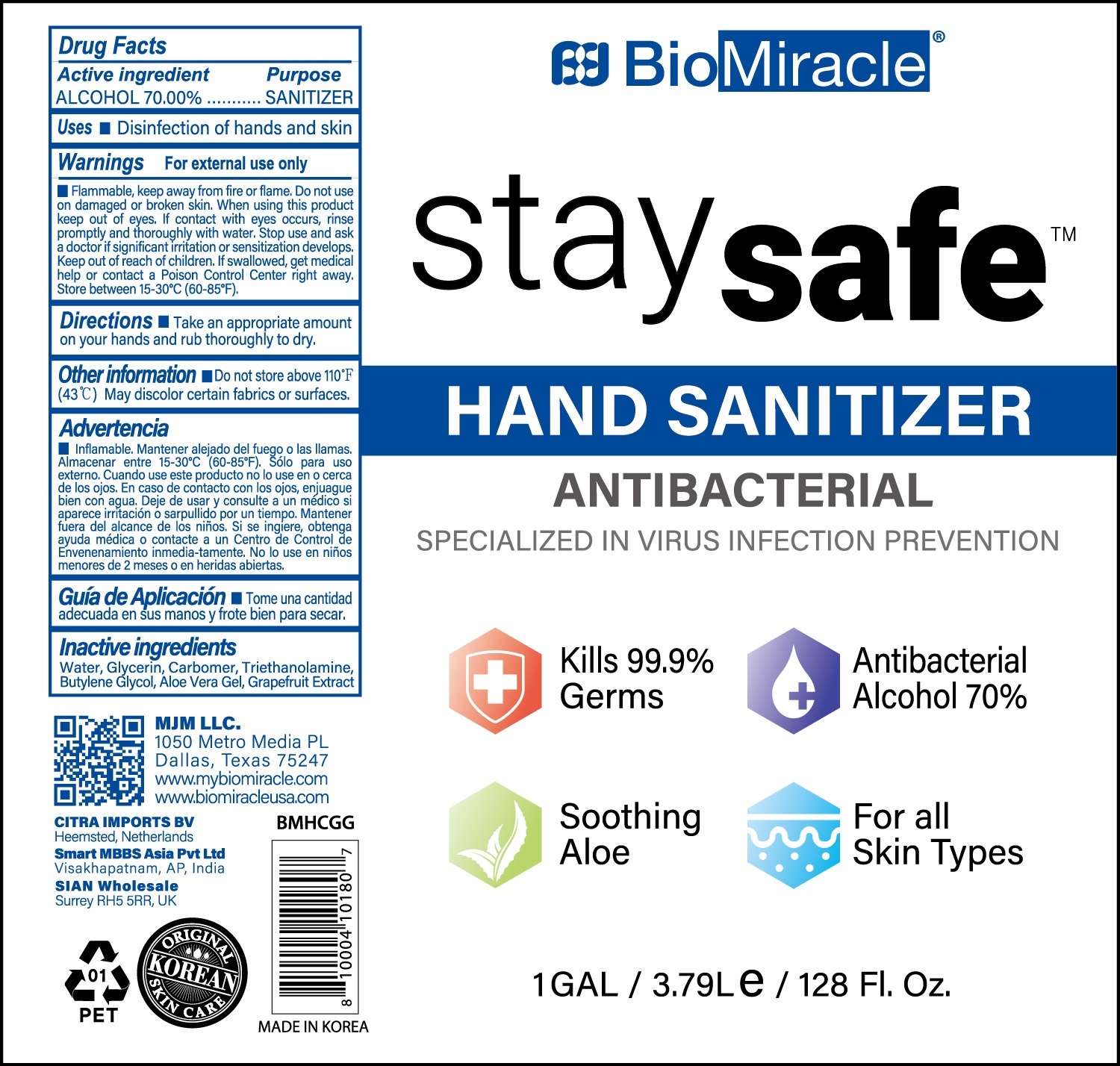 DRUG LABEL: BioMiracle staysafe HAND SANITIZER
NDC: 77978-108 | Form: GEL
Manufacturer: MJM SOURCING, LLC
Category: otc | Type: HUMAN OTC DRUG LABEL
Date: 20200713

ACTIVE INGREDIENTS: ALCOHOL 2649 mL/3785 mL
INACTIVE INGREDIENTS: GLYCERIN; WATER; CARBOMER HOMOPOLYMER, UNSPECIFIED TYPE; TROLAMINE; BUTYLENE GLYCOL; ALOE VERA LEAF; GRAPEFRUIT

[Manufacturer:WHITE COSPHARM CO.,LTD.]
[Labeler : MJM SOURCING, LLC]
77978-108-01
BioMiracle staysafe HAND SANITIZER